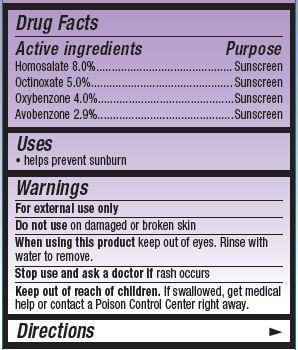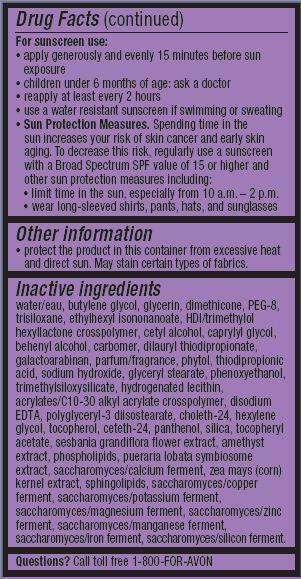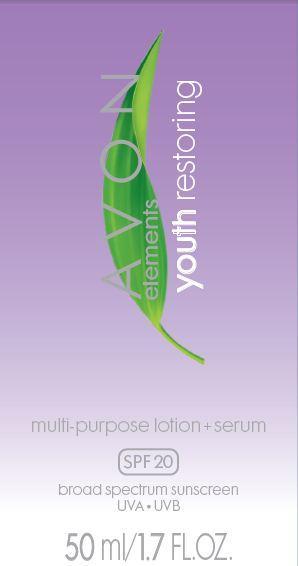 DRUG LABEL: Avon Elements
NDC: 10096-0318 | Form: LOTION
Manufacturer: New Avon LLC
Category: otc | Type: HUMAN OTC DRUG LABEL
Date: 20160219

ACTIVE INGREDIENTS: HOMOSALATE 80 mg/1 mL; OCTINOXATE 50 mg/1 mL; OXYBENZONE 40 mg/1 mL; AVOBENZONE 29 mg/1 mL

Active Ingredients
Homosalate 8.0%............................
Octinoxate 5.0%..............................
Oxybenzone 4.0%...........................
Avobenzone 2.9%...........................

Purpose
............... Sunscreen
............... Sunscreen
.............. Sunscreen

.............. Sunscreen

Uses

- helps prevent sunburn

Warnings
For external use only

Do not use on damaged or broken skin

When using this product keep out of eyes. Rinse with water to remove.

Stop use and ask a doctor if rash occurs

Keep out of reach of children. If swallowed, get medical help or contact a Poison Control Center right away.

Directions

For sunscreen use:

- apply generously and evenly 15 minutes before sun exposure
- children under 6 month of age:ask a doctor
- reapply at least every 2 hours
- use a water resistant sunscreen if swimming or sweating
- Sun Protection Measures. Spending time in the sun increases your risk of skin cancer and early skin aging. To decrease this risk, regularly use a sunscreen with a Broad Spectrum SPF value of 15 or higher and other sun protection measures including:
  • limit time in the sun, especially from 10 a.m. – 2 p.m.
  • wear long-sleeved shirts, pants, hats, and sunglasses

Other Information

- protect the product in this container from excessive heat and direct sun. May stain certain types of fabrics.

Inactive ingredients:
water/eau, butylene glycol, glycerin, dimethicone, PEG-8, trisiloxane, ethylhexyl isononanoate, HDI/trimethylol hexyllactone crosspolymer, cetyl alcohol, caprylyl glycol, behenyl alcohol, carbomer, dilauryl thiodipropionate, galactoarabinan, parfum/fragrance, phytol, thiodipropionic
acid, sodium hydroxide, glyceryl stearate, phenoxyethanol, trimethylsiloxysilicate, hydrogenated lecithin, acrylates/C10-30 alkyl acrylate crosspolymer, disodium EDTA, polyglyceryl-3 diisostearate, choleth-24, hexylene glycol, tocopherol, ceteth-24, panthenol, silica, tocopheryl
acetate, sesbania grandiflora flower extract, amethyst extract, phospholipids, pueraria lobata symbiosome extract, saccharomyces/calcium ferment, zea mays (corn) kernel extract, sphingolipids, saccharomyces/copper ferment, saccharomyces/potassium ferment, saccharomyces/magnesium ferment, saccharomyces/zinc ferment, saccharomyces/manganese ferment, saccharomyces/iron ferment, saccharomyces/silicon ferment.

Questions?
Call toll free 1-800-FOR-AVON